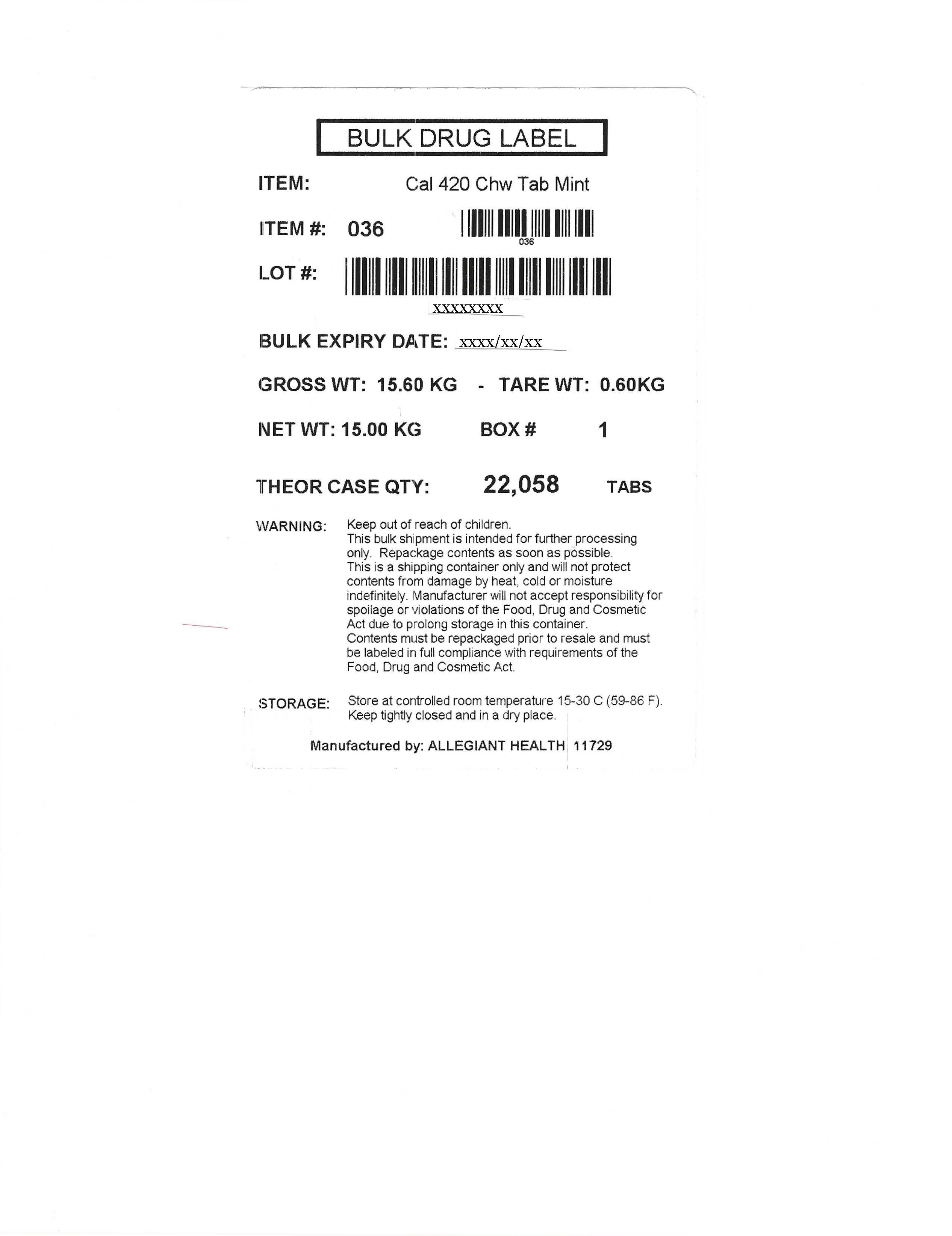 DRUG LABEL: Calcium Carbonate
NDC: 69168-036 | Form: TABLET, CHEWABLE
Manufacturer: Allegiant Health
Category: otc | Type: HUMAN OTC DRUG LABEL
Date: 20250228

ACTIVE INGREDIENTS: CALCIUM CARBONATE 420 mg/1 1
INACTIVE INGREDIENTS: ASPARTAME; CROSCARMELLOSE SODIUM; MAGNESIUM STEARATE; MALTODEXTRIN; SORBITOL

036 - Calcium Carbonate 420mg

Active ingredient(s)

Calcium Carbonate 420mg

Purpose

Antacid

Use(s)

relieves

- heartburn
- sour stomach
- acid indigestion
- upset stomach due to these symptoms

Warnings

Ask a doctor or pharmacist before use if you

- have kidney disease
- are taking a prescription drug
  Antacids may interact with certain prescription drugs

When using this product

do not take more than 19 tablets in a 24 hour period or use the maximum dosage
of this product for more than two weeks except under the advice and supervision of a doctor. If symptoms
persist for more than two weeks, stop using this product and see a doctor.

Directions

- chew 2 tablets every 2-3 hours or as symptoms occur, repeat hourly if needed

Other information

- each tablet contains: calcium 168mg
- Phenylketonurics: Contains phenylalanine 1.5 mg per tablet
- store at 15°- 30°C (59°-86°F)
- do not use if imprinted safety seal under cap is broken or missing

Inactive ingredients

aspartame, croscarmellose sodium, magnesium stearate, maltodextrin, mint flavor, sorbitol

Questions/Comments

Call 1-888-952-0050

Monday through Friday 9AM to 5PM EST.

Principal Display Panel

Calcium Carbonate 420mg